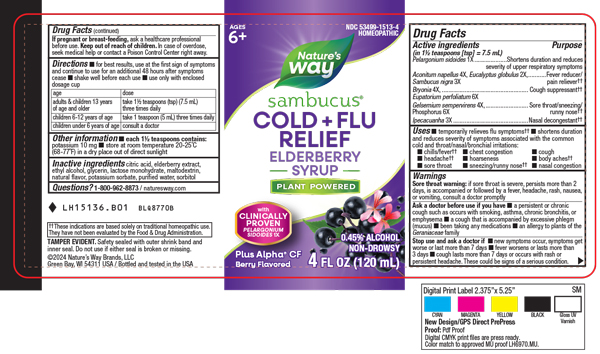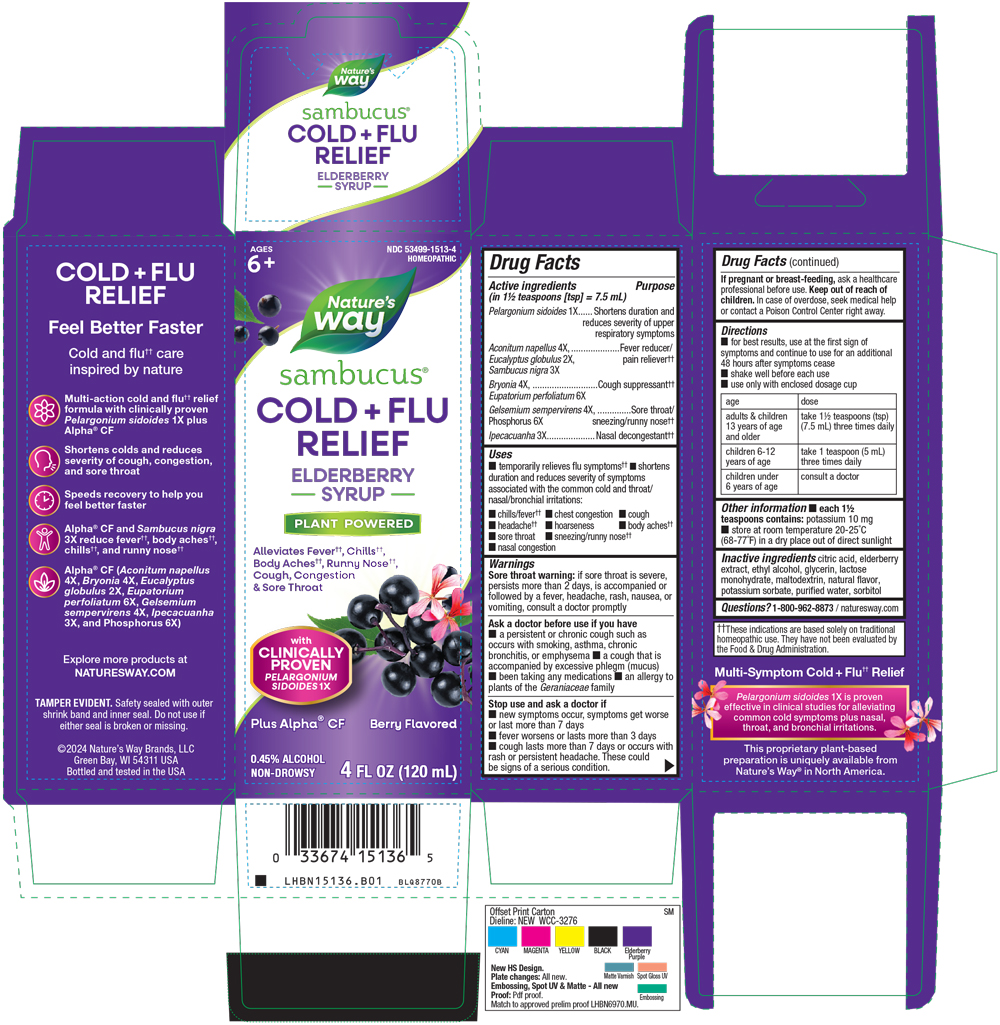 DRUG LABEL: Sambucus Cold Flu Relief Elderberry
NDC: 53499-1513 | Form: SYRUP
Manufacturer: Schwabe North America
Category: homeopathic | Type: HUMAN OTC DRUG LABEL
Date: 20251022

ACTIVE INGREDIENTS: PELARGONIUM SIDOIDES ROOT 1 [hp_X]/120 mL; ACONITUM NAPELLUS 4 [hp_X]/120 mL; EUCALYPTUS GLOBULUS LEAF 2 [hp_X]/120 mL; SAMBUCUS NIGRA FLOWERING TOP 3 [hp_X]/120 mL; BRYONIA ALBA ROOT 4 [hp_X]/120 mL; EUPATORIUM PERFOLIATUM FLOWERING TOP 6 [hp_X]/120 mL; GELSEMIUM SEMPERVIRENS ROOT 4 [hp_X]/120 mL; IPECAC 3 [hp_X]/120 mL; PHOSPHORUS 6 [hp_X]/120 mL
INACTIVE INGREDIENTS: ANHYDROUS CITRIC ACID; EUROPEAN ELDERBERRY; ALCOHOL; GLYCERIN; LACTOSE MONOHYDRATE; MALTODEXTRIN; WATER; SORBITOL; POTASSIUM SORBATE

Sambucus Cold + Flu Relief Elderberry Syrup

Active Ingredients

Pelargonium sidoides 1x

Aconitum napellus 4x

Eucalyptus globulus 2x

Sambucus nigra 3x

Bryonia 4x

Eupatorium perfoliatum 6x

Gelsemium sempervirens 4x

Phosphorus 6x

Ipecacuanha 3x

Inactive Ingredients

Citric Acid

Elderberry Extract

Ethyl Alcohol

Glycerin

Lactose Monohydrate

Maltodextrin

Natural Flavor

Potassium Sorbate

Purified Water

Sorbitol

Indications & Usage

Temporarily relieves flu symptoms. Shortens duration and reduces severity of symptoms associated with the common cold and throat/nasal/bronchial irritations: chills/fever, chest congestion, cough, headache, hoarseness, body aches, sore throat, sneezing/runny nose, nasal congestion.

Dosage & Administration

Directions:

For best results, use at first sign of symptoms and continue to use for an additional 48 hours after symptoms cease.

Shake well before each use.

Use only with enclosed dosage cup.
Adults & children 13 years of age and older: take 1½ teaspoons (tsp) (7.5 mL) three times daily.
Children 6 to 12 years of age: take 1 teaspoon (tsp) (5mL) three times daily.
Children under 6 years of age: consult a doctor.

Purpose

Temporarily relieves flu symptoms. Shortens duration and reduces severity of symptoms associated with the common cold and throat/nasal/bronchial irritations: chills/fever, chest congestion, cough, headache, hoarseness, body aches, sore throat, sneezing/runny nose, nasal congestion.

Warnings

Sore throat warning: if sore throat is severe, persists more than 2 days, is accompanied or followed by a fever, headache, rash, nausea, or vomiting, consult a doctor promptly.

Ask Doctor

Ask a doctor before use if you have a persistent or chronic cough such as occurs with smoking, asthma, chronic bronchitis or emphysema, a cough that is accompanied by excessive phlegm (mucus), been taking any medications, an allergy to plants of the Geraniaceae family.

Stop Use

Stop use and ask a doctor if new symptoms occur, symptoms get worse or last more than 7 days, fever worsens or lasts more than 3 days, cough lasts more then 7 days or occurs with rash or persistent headache.

These could be signs of a serious condition.

Pregnancy or Breastfeeding

If pregnant or breast-feeding, ask a healthcare professional before use.

Keep out of reach of children

Overdose

In case of overdose, seek medical help or contact a Poison Control Center right away.